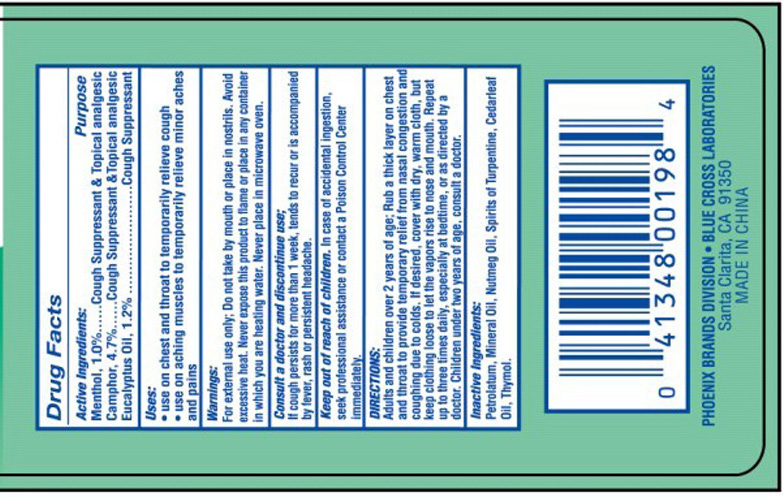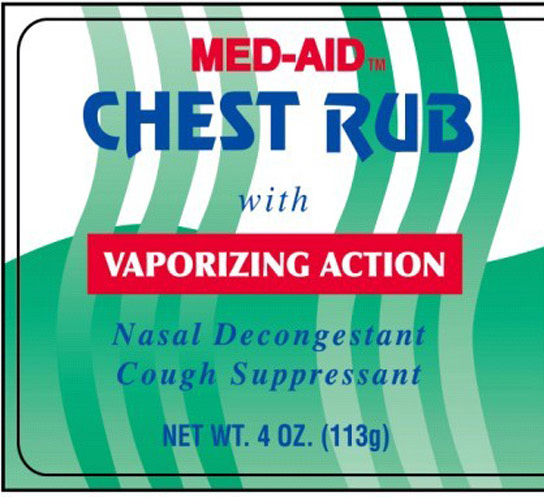 DRUG LABEL: Med Aid
NDC: 22431-125 | Form: OINTMENT
Manufacturer: Blue Cross Laboratories, Inc.
Category: otc | Type: HUMAN OTC DRUG LABEL
Date: 20120403

ACTIVE INGREDIENTS: MENTHOL 1.0 g/100 g; CAMPHOR (SYNTHETIC) 4.7 g/100 g; EUCALYPTUS OIL 1.2 g/100 g
INACTIVE INGREDIENTS: PETROLATUM; MINERAL OIL; NUTMEG OIL; TURPENTINE; CEDAR LEAF OIL; THYMOL

Med-Aid Chest Rub

Active Ingredients Purpose

Menthol 1.0% Cough Suppressant and Topical Analgesic

Camphor 4.7% Cough Suppressant and Topical Analgesic

Eucalyptus Oil 1.2% Cough suppressant

Uses:

Use on chest and throat to temporarily relieve cough.

Use on aching muscles to temporarily relieve minor aches and pains

Keep out of reach of children.In case of accidental ingestion, seek professional assistance or contact a Poison Control Center immediately.

INDICATIONS AND USAGE

Consult a doctor and discontinue use;

If cough persists more than 1 week, tends to recur or is accompanied by fever rash or persistent headache.

Warnings:

For external use only; Do not take by mouth or place in nostrils. Avoid excessive heat. Never expose this product to flame or place in any container in which you are heating water. Never place in microwave oven.

Directions

Adults and children over 2 years of age: Rub a thick layer on chest throat to provide temporary relief from nasal congestion and coughing due to colds. If desired, cover with dry warm cloth and clothing loose to let the vapors rise to nose and mouth. Repeat up to three times daily, especially at bed time, or as directed by a doctor Children under two years of age, consult a doctor.

Inactive ingredients:

Petrolatum, Mineral Oil, Nutmeg Oil, Spirits of Turpentine, Cedarleaf Oil, Thymol.

PACKAGE LABEL

Med-Aid

Chest Rub

with vaporizing action

Nasal decongestant
Cough Suppressant
Net. Wt. 4.oz. (113g)